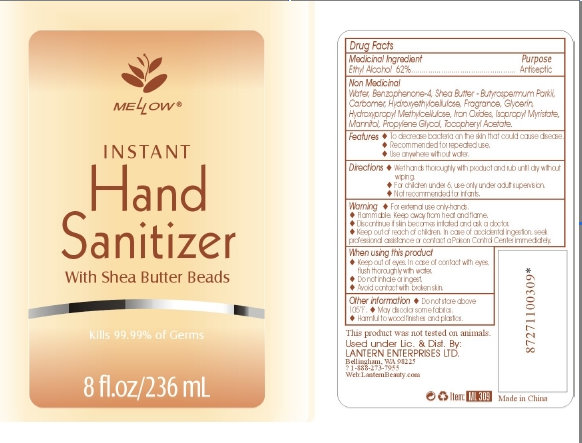 DRUG LABEL: Instant Hand Sanitizer With Shea Butter Beads
NDC: 50154-4000 | Form: GEL
Manufacturer: Lantern Enterprises Ltd
Category: otc | Type: HUMAN OTC DRUG LABEL
Date: 20100604

ACTIVE INGREDIENTS: ALCOHOL 62 mL/100 mL
INACTIVE INGREDIENTS: WATER; SULISOBENZONE; GLYCERIN; ISOPROPYL MYRISTATE; MANNITOL; PROPYLENE GLYCOL

Instant Hand Sanitizer With Shea Butter Beads

Medicinal Ingredient Purpose
Ethyl Alcohol 62%........................................Antiseptic

PURPOSE

Features

To decrease bacteria on the skin that could cause disease
Recommended for repeated use.
Use anywhere without water.

Warning

For external use only-hands.
May discolor some fabrics.
Harmful to wood finishes and plastics.

STORAGE AND HANDLING

Flammable, Keep away from heat and flame.
Do not store above 105 degree Fahrenheit.

STOP USE

Discontinue if skin becomes irritated and ask a doctor.

Keep out of reach of children. In case of accidental ingestion, seek professional assistance or contact a Poison Control Center immediately.

INACTIVE INGREDIENT

Non Medicinal
Water, Benzophenone-4, Shea Butter - Butyrospermum Parkii, Carbomer, Hydroxyethylcellulose, Fragrance, Glycerin, Hydroxypropyl Methylcellulose, Iron Oxides, Isopropyl Myristate, Mannitol, Propylene Glycol, Tocopheryl Acetate.

Directions
Wet hands thoroughly with product and rub until dry without wiping.
For children under 6, use only under adult supervision.
Not recommended for infants.

WHEN USING

Keep out of eyes. In case of contact with eyes, flush thoroughly with water.
Do not inhale or ingest.
Avoid contact with broken skin.

DESCRIPTION

This product was not tested on animals.
Made in China Item : ML 308
87271100308
Use under Lic. and Dist. By:
LANTERN ENTERPRISES LTD.
Bellingham, WA 98225
? 1-888-273-7955
Web: LanternBeauty.com

PACKAGE LABEL

MELLOW
INSTANT Hand Sanitizer
With Shea Butter Beads
Kills 99.99% of Germs
2 fl.oz/59 mL